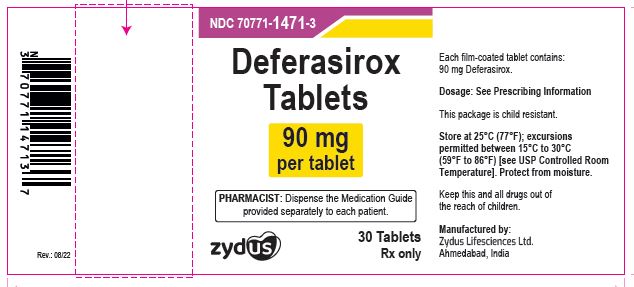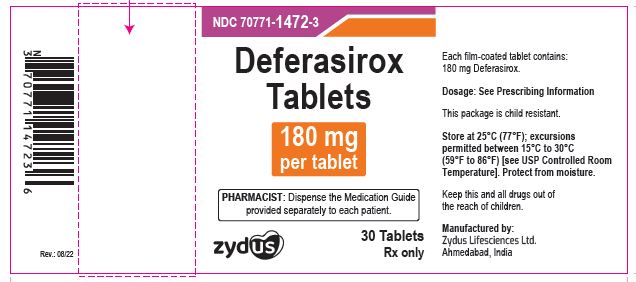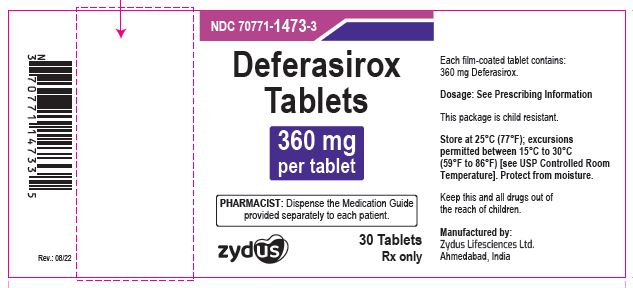 DRUG LABEL: deferasirox
NDC: 70771-1471 | Form: TABLET, FILM COATED
Manufacturer: Zydus Lifesciences Limited
Category: prescription | Type: HUMAN PRESCRIPTION DRUG LABEL
Date: 20241126

ACTIVE INGREDIENTS: DEFERASIROX 90 mg/1 1
INACTIVE INGREDIENTS: CROSCARMELLOSE SODIUM; HYPROMELLOSE 2910 (6 MPA.S); MAGNESIUM STEARATE; MICROCRYSTALLINE CELLULOSE; POLOXAMER 407; POLYETHYLENE GLYCOL 8000; POVIDONE K30; SILICON DIOXIDE; TALC; TITANIUM DIOXIDE

DEFERASIROX TABLETS

PACKAGE LABEL.PRINCIPAL DISPLAY PANEL

NDC 70771-1471-3

Deferasirox tablets, 90 mg

30 Tablets

Rx only

NDC 70771-1472-3

Deferasirox tablets, 180 mg

30 Tablets

Rx only

NDC 70771-1473-3

Deferasirox tablets, 360 mg

30 Tablets

Rx only